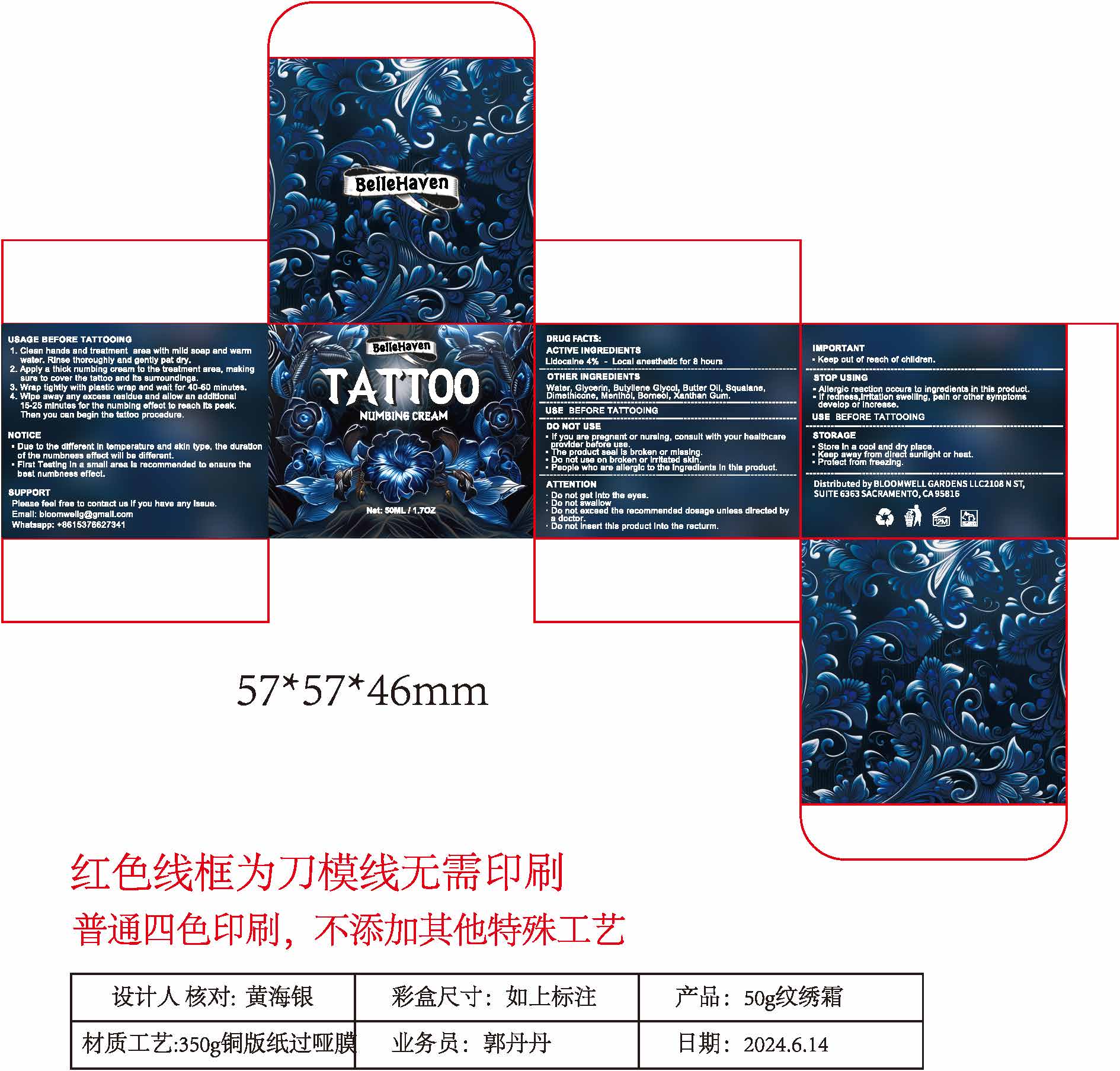 DRUG LABEL: Tattoo numbing cream
NDC: 85284-001 | Form: CREAM
Manufacturer: BLOOMWELL GARDENS LLC
Category: otc | Type: HUMAN OTC DRUG LABEL
Date: 20250226

ACTIVE INGREDIENTS: LIDOCAINE 4 g/100 g
INACTIVE INGREDIENTS: SQUALANE; RICE GERM; PRILOCAINE; SIMMONDSIA CHINENSIS (JOJOBA) SEED OIL; MENTHOL; ALOE BARBADENSIS LEAF; PROCAINE; GLYCERYL STEARATE; XANTHAN GUM; DIMETHICONE; GLYCERIN; SHEANUT OIL; CETEARYL GLUCOSIDE; MENTHA ARVENSIS LEAF; BUTYLENE GLYCOL; CENTELLA ASIATICA ROOT; SODIUM HYALURONATE; TOCOPHEROL; TETRACAINE; CETEARYL ALCOHOL; BORNEOL

ACTIVE INGREDIENT

Lidocaine 4% - Local anesthetic for 8 hours

PURPOSE

External Analgesic

DOSAGE & ADMINISTRATION

- Due to the different in temprature and skin type, the duration of the numbness effect will be different.
- First test in a small area is recommended to ensure the best numbness effect.

USEAGE BEFORE TATTOOING

1. Clean hands and treatment are with mild soap and warm water. Rinse thoroughly and gently pat dry.

2. Apply a thick numbing cream to the treatment area, making sure to cover the tattoo and its surroundings.

3. Wrap tightly with plastic wrap and wait for 40-60 munutes.

4. Wipe away any exceess residue and allow addtional 15-25 minutes for the numbing effect to reach its peak. Then you can begin the tattoo procedure.

DO NOT USE

- If you are pregnant or nursing, consult with your healthcare provider before use.
- The product seal is broken or missing.
- Do not use on broken or irritated skin.
- People who are allergic to the ingredients in this product.

ATTENTION

- Do not get into eyes.
- Do not swallow.
- Do not exceed the recommended dosage unless directed by a doctor.
- Do not insert this product into the recturm.

IMPORTANT

Keep out of reach of children.

OTHER INGREDIENTS

Water, Glycerin, Butyllene Glycol, Butter Oil, Squalane, Dimethicone, Menthol, Borneol, Xanthan Gum.